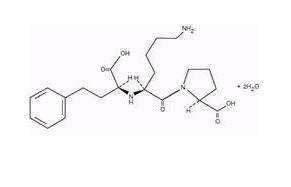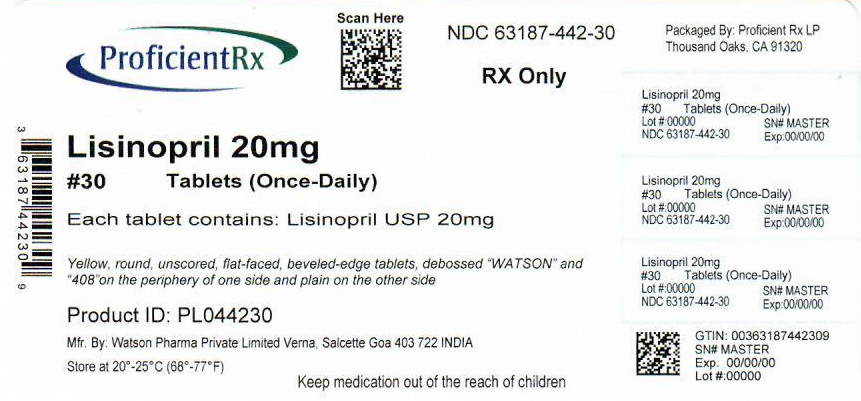 DRUG LABEL: Lisinopril
NDC: 63187-442 | Form: TABLET
Manufacturer: Proficient Rx LP
Category: prescription | Type: HUMAN PRESCRIPTION DRUG LABEL
Date: 20220401

ACTIVE INGREDIENTS: LISINOPRIL 20 mg/1 1
INACTIVE INGREDIENTS: SILICON DIOXIDE; DIBASIC CALCIUM PHOSPHATE DIHYDRATE; MAGNESIUM STEARATE; MANNITOL; STARCH, CORN; FD&C YELLOW NO. 5; ALUMINUM OXIDE

ONCE-DAILY
Lisinopril Tablets USP
Revised: January 2014
Rx only

WARNING: FETAL TOXICITY

See full prescribing information for complete boxed warning.

- When pregnancy is detected, discontinue lisinopril as soon as possible.
- Drugs that act directly on the renin-angiotensin system can cause injury and death to the developing fetus. See Warnings: Fetal Toxicity.

DESCRIPTION

Lisinopril is an oral long-acting angiotensin converting enzyme inhibitor. Lisinopril, a synthetic peptide derivative, is chemically described as (S)-1-[N^2-(1-carboxy-3-phenylpropyl)-L-lysyl]-L-proline dihydrate. Its empirical formula is C21H31N3O5•2H2O and its structural formula is:

Lisinopril is a white to off-white, crystalline powder, with a molecular weight of 441.53. It is soluble in water and sparingly soluble in methanol and practically insoluble in ethanol.

Lisinopril is supplied as 2.5 mg, 5 mg, 10 mg, 20 mg, 30 mg and 40 mg tablets for oral administration.

Each tablet for oral administration contains 2.5 mg, 5 mg, 10 mg, 20 mg, 30 mg, or 40 mg of lisinopril USP. In addition, each tablet contains the following inactive ingredients: colloidal silicon dioxide, dibasic calcium phosphate, FD&C Blue #2 Aluminum Lake (10 mg only), FD&C Yellow #5 Aluminum Lake (20 mg, 30 mg, and 40 mg, only), magnesium stearate, mannitol, pregelatinized starch.

CLINICAL PHARMACOLOGY

Mechanism of Action: Lisinopril inhibits angiotensin-converting enzyme (ACE) in human subjects and animals. ACE is a peptidyl dipeptidase that catalyzes the conversion of angiotensin I to the vasoconstrictor substance, angiotensin II. Angiotensin II also stimulates aldosterone secretion by the adrenal cortex. The beneficial effects of lisinopril in hypertension and heart failure appear to result primarily from suppression of the renin-angiotensin-aldosterone system. Inhibition of ACE results in decreased plasma angiotensin II which leads to decreased vasopressor activity and to decreased aldosterone secretion. The latter decrease may result in a small increase of serum potassium. In hypertensive patients with normal renal function treated with lisinopril alone for up to 24 weeks, the mean increase in serum potassium was approximately 0.1 mEq/L; however, approximately 15% of patients had increases greater than 0.5 mEq/L and approximately 6% had a decrease greater than 0.5 mEq/L. In the same study, patients treated with lisinopril and hydrochlorothiazide for up to 24 weeks had a mean decrease in serum potassium of 0.1 mEq/L; approximately 4% of patients had increases greater than 0.5 mEq/L and approximately 12% had a decrease greater than 0.5 mEq/L (See PRECAUTIONS). Removal of angiotensin II negative feedback on renin secretion leads to increased plasma renin activity.

ACE is identical to kininase, an enzyme that degrades bradykinin. Whether increased levels of bradykinin, a potent vasodepressor peptide, play a role in the therapeutic effects of lisinopril remains to be elucidated.

While the mechanism through which lisinopril lowers blood pressure is believed to be primarily suppression of the renin-angiotensin-aldosterone system, lisinopril is antihypertensive even in patients with low-renin hypertension. Although lisinopril was antihypertensive in all races studied, Black hypertensive patients (usually a low-renin hypertensive population) had a smaller average response to monotherapy than non-Black patients.

Concomitant administration of lisinopril and hydrochlorothiazide further reduced blood pressure in Black and non-Black patients and any racial differences in blood pressure response were no longer evident.

Pharmacokinetics and Metabolism:

Adult Patients: Following oral administration of lisinopril, peak serum concentrations of lisinopril occur within about 7 hours, although there was a trend to a small delay in time taken to reach peak serum concentrations in acute myocardial infarction patients. Declining serum concentrations exhibit a prolonged terminal phase which does not contribute to drug accumulation. This terminal phase probably represents saturable binding to ACE and is not proportional to dose.

Lisinopril does not appear to be bound to other serum proteins. Lisinopril does not undergo metabolism and is excreted unchanged entirely in the urine. Based on urinary recovery, the mean extent of absorption of lisinopril is approximately 25%, with large intersubject variability (6% to 60%) at all doses tested (5 to 80 mg). Lisinopril absorption is not influenced by the presence of food in the gastrointestinal tract. The absolute bioavailability of lisinopril is reduced to 16% in patients with stable NYHA Class II-IV congestive heart failure, and the volume of distribution appears to be slightly smaller than that in normal subjects. The oral bioavailability of lisinopril in patients with acute myocardial infarction is similar to that in healthy volunteers.

Upon multiple dosing, lisinopril exhibits an effective half-life of accumulation of 12 hours.

Impaired renal function decreases elimination of lisinopril, which is excreted principally through the kidneys, but this decrease becomes clinically important only when the glomerular filtration rate is below 30 mL/min. Above this glomerular filtration rate, the elimination half-life is little changed. With greater impairment, however, peak and trough lisinopril levels increase, time to peak concentration increases and time to attain steady state is prolonged. Older patients, on average, have (approximately doubled) higher blood levels and area under the plasma concentration time curve (AUC) than younger patients (See DOSAGE AND ADMINISTRATION). Lisinopril can be removed by hemodialysis.

Studies in rats indicate that lisinopril crosses the blood-brain barrier poorly. Multiple doses of lisinopril in rats do not result in accumulation in any tissues. Milk of lactating rats contains radioactivity following administration of ^14C lisinopril. By whole body autoradiography, radioactivity was found in the placenta following administration of labeled drug to pregnant rats, but none was found in the fetuses.

Pediatric Patients: The pharmacokinetics of lisinopril were studied in 29 pediatric hypertensive patients between 6 years and 16 years with glomerular filtration rate > 30 mL/min/1.73 m^2. After doses of 0.1 to 0.2 mg/kg, steady state peak plasma concentrations of lisinopril occurred within 6 hours and the extent of absorption based on urinary recovery was about 28%. These values are similar to those obtained previously in adults. The typical value of lisinopril oral clearance (systemic clearance/absolute bioavailability) in a child weighing 30 kg is 10 L/h, which increases in proportion to renal function.

Pharmacodynamics and Clinical Effects

Hypertension:

Adult Patients: Administration of lisinopril to patients with hypertension results in a reduction of both supine and standing blood pressure to about the same extent with no compensatory tachycardia. Symptomatic postural hypotension is usually not observed although it can occur and should be anticipated in volume and/or salt-depleted patients (See WARNINGS). When given together with thiazide-type diuretics, the blood pressure lowering effects of the two drugs are approximately additive.

In most patients studied, onset of antihypertensive activity was seen at one hour after oral administration of an individual dose of lisinopril, with peak reduction of blood pressure achieved by 6 hours. Although an antihypertensive effect was observed 24 hours after dosing with recommended single daily doses, the effect was more consistent and the mean effect was considerably larger in some studies with doses of 20 mg or more than with lower doses; however, at all doses studied, the mean antihypertensive effect was substantially smaller 24 hours after dosing than it was 6 hours after dosing.

In some patients achievement of optimal blood pressure reduction may require two to four weeks of therapy.

The antihypertensive effects of lisinopril are maintained during long-term therapy. Abrupt withdrawal of lisinopril has not been associated with a rapid increase in blood pressure, or a significant increase in blood pressure compared to pretreatment levels.

Two dose-response studies utilizing a once-daily regimen were conducted in 438 mild to moderate hypertensive patients not on a diuretic. Blood pressure was measured 24 hours after dosing. An antihypertensive effect of lisinopril was seen with 5 mg in some patients. However, in both studies blood pressure reduction occurred sooner and was greater in patients treated with 10, 20 or 80 mg of lisinopril. In controlled clinical studies, lisinopril 20 to 80 mg has been compared in patients with mild to moderate hypertension to hydrochlorothiazide 12.5 to 50 mg and with atenolol 50 to 200 mg; and in patients with moderate to severe hypertension to metoprolol 100 to 200 mg. It was superior to hydrochlorothiazide in effects on systolic and diastolic pressure in a population that was 3/4 Caucasian. Lisinopril was approximately equivalent to atenolol and metoprolol in effects on diastolic blood pressure, and had somewhat greater effects on systolic blood pressure.

Lisinopril had similar effectiveness and adverse effects in younger and older (> 65 years) patients. It was less effective in Blacks than in Caucasians.

In hemodynamic studies in patients with essential hypertension, blood pressure reduction was accompanied by a reduction in peripheral arterial resistance with little or no change in cardiac output and in heart rate. In a study in nine hypertensive patients, following administration of lisinopril, there was an increase in mean renal blood flow that was not significant. Data from several small studies are inconsistent with respect to the effect of lisinopril on glomerular filtration rate in hypertensive patients with normal renal function, but suggest that changes, if any, are not large.

In patients with renovascular hypertension lisinopril has been shown to be well tolerated and effective in controlling blood pressure (See PRECAUTIONS).

Pediatric Patients: In a clinical study involving 115 hypertensive pediatric patients 6 to 16 years of age, patients who weighed < 50 kg received either 0.625, 2.5 or 20 mg of lisinopril daily and patients who weighed ≥ 50 kg received either 1.25, 5, or 40 mg of lisinopril daily. At the end of 2 weeks, lisinopril administered once daily lowered trough blood pressure in a dose-dependent manner with consistent antihypertensive efficacy demonstrated at doses > 1.25 mg (0.02 mg/kg). This effect was confirmed in a withdrawal phase, where the diastolic pressure rose by about 9 mmHg more in patients randomized to placebo than it did in patients who were randomized to remain on the middle and high doses of lisinopril. The dose-dependent antihypertensive effect of lisinopril was consistent across several demographic subgroups: age, Tanner stage, gender, and race. In this study, lisinopril was generally well-tolerated.

In the above pediatric studies, lisinopril was given either as tablets or in a suspension for those children and infants who were unable to swallow tablets or who required a lower dose than is available in tablet form (See DOSAGE AND ADMINISTRATION).

Heart Failure:

During baseline-controlled clinical trials, in patients receiving digitalis and diuretics, single doses of lisinopril resulted in decreases in pulmonary capillary wedge pressure, systemic vascular resistance and blood pressure accompanied by an increase in cardiac output and no change in heart rate.

In two placebo controlled, 12-week clinical studies using doses of lisinopril up to 20 mg, lisinopril as adjunctive therapy to digitalis and diuretics improved the following signs and symptoms due to congestive heart failure: edema, rales, paroxysmal nocturnal dyspnea and jugular venous distention. In one of the studies, beneficial response was also noted for: orthopnea, presence of third heart sound and the number of patients classified as NYHA Class III and IV. Exercise tolerance was also improved in this study. The once-daily dosing for the treatment of congestive heart failure was the only dosage regimen used during clinical trial development and was determined by the measurement of hemodynamic response. A large (over 3000 patients) survival study, the ATLAS Trial, comparing 2.5 mg and 35 mg of lisinopril in patients with heart failure, showed that the higher dose of lisinopril had outcomes at least as favorable as the lower dose.

Acute Myocardial Infarction:

The Gruppo Italiano per lo Studio della Sopravvienza nell’Infarto Miocardico (GISSI-3) study was a multicenter, controlled, randomized, unblinded clinical trial conducted in 19,394 patients with acute myocardial infarction admitted to a coronary care unit. It was designed to examine the effects of short-term (6 week) treatment with lisinopril, nitrates, their combination, or no therapy on short-term (6 week) mortality and on long-term death and markedly impaired cardiac function. Patients presenting within 24 hours of the onset of symptoms who were hemodynamically stable were randomized, in a 2 x 2 factorial design, to six weeks of either 1) lisinopril alone (n=4841), 2) nitrates alone (n=4869), 3) lisinopril plus nitrates (n=4841), or 4) open control (n=4843). All patients received routine therapies, including thrombolytics (72%), aspirin (84%), and a beta-blocker (31%), as appropriate, normally utilized in acute myocardial infarction (MI) patients.

The protocol excluded patients with hypotension (systolic blood pressure ≤ 100 mmHg), severe heart failure, cardiogenic shock, and renal dysfunction (serum creatinine > 2 mg/dL and/or proteinuria > 500 mg/24 h). Doses of lisinopril were adjusted as necessary according to protocol (See DOSAGE AND ADMINISTRATION).

Study treatment was withdrawn at six weeks except where clinical conditions indicated continuation of treatment.

The primary outcomes of the trial were the overall mortality at 6 weeks and a combined end point at 6 months after the myocardial infarction, consisting of the number of patients who died, had late (day 4) clinical congestive heart failure, or had extensive left ventricular damage defined as ejection fraction ≤ 35% or an akinetic-dyskinetic [A-D] score ≥ 45%. Patients receiving lisinopril (n=9646), alone or with nitrates, had an 11% lower risk of death (2p [two-tailed] = 0.04) compared to patients receiving no lisinopril (n=9672) (6.4% vs. 7.2%, respectively) at six weeks. Although patients randomized to receive lisinopril for up to six weeks also fared numerically better on the combined end point at 6 months, the open nature of the assessment of heart failure, substantial loss to follow-up echocardiography, and substantial excess use of lisinopril between 6 weeks and 6 months in the group randomized to 6 weeks of lisinopril, preclude any conclusion about this end point.

Patients with acute myocardial infarction, treated with lisinopril, had a higher (9.0% versus 3.7%) incidence of persistent hypotension (systolic blood pressure < 90 mmHg for more than 1 hour) and renal dysfunction (2.4% versus 1.1%) in-hospital and at six weeks (increasing creatinine concentration to over 3 mg/dL or a doubling or more of the baseline serum creatinine concentration). See ADVERSE REACTIONS - Acute Myocardial Infarction.

INDICATIONS AND USAGE

Hypertension: Lisinopril tablets are indicated for the treatment of hypertension to lower blood pressure. Lowering blood pressure lowers the risk of fatal and non-fatal cardiovascular events, primarily strokes and myocardial infarctions. These benefits have been seen in controlled trials of antihypertensive drugs from a wide variety of pharmacologic classes including lisinopril.

Control of high blood pressure should be part of comprehensive cardiovascular risk management, including, as appropriate, lipid control, diabetes management, antithrombotic therapy, smoking cessation, exercise, and limited sodium intake. Many patients will require more than 1 drug to achieve blood pressure goals. For specific advice on goals and management, see published guidelines, such as those of the National High Blood Pressure Education Program’s Joint National Committee on Prevention, Detection, Evaluation, and Treatment of High Blood Pressure (JNC).

Numerous antihypertensive drugs, from a variety of pharmacologic classes and with different mechanisms of action, have been shown in randomized controlled trials to reduce cardiovascular morbidity and mortality, and it can be concluded that it is blood pressure reduction, and not some other pharmacologic property of the drugs, that is largely responsible for those benefits. The largest and most consistent cardiovascular outcome benefit has been a reduction in the risk of stroke, but reductions in myocardial infarction and cardiovascular mortality also have been seen regularly.

Elevated systolic or diastolic pressure causes increased cardiovascular risk, and the absolute risk increase per mmHg is greater at higher blood pressures, so that even modest reductions of severe hypertension can provide substantial benefit. Relative risk reduction from blood pressure reduction is similar across populations with varying absolute risk, so the absolute benefit is greater in patients who are at higher risk independent of their hypertension (for example, patients with diabetes or hyperlipidemia), and such patients would be expected to benefit from more aggressive treatment to a lower blood pressure goal.

Some antihypertensive drugs have smaller blood pressure effects (as monotherapy) in black patients, and many antihypertensive drugs have additional approved indications and effects (e.g., on angina, heart failure, or diabetic kidney disease). These considerations may guide selection of therapy.

Lisinopril tablets USP may be administered alone or with other antihypertensive agents.

Heart Failure: Lisinopril tablets USP are indicated as adjunctive therapy in the management of heart failure in patients who are not responding adequately to diuretics and digitalis.

Acute Myocardial Infarction: Lisinopril tablets USP are indicated for the treatment of hemodynamically stable patients within 24 hours of acute myocardial infarction, to improve survival. Patients should receive, as appropriate, the standard recommended treatments such as thrombolytics, aspirin and beta-blockers.

In using lisinopril tablets USP, consideration should be given to the fact that another angiotensin-converting enzyme inhibitor, captopril, has caused agranulocytosis, particularly in patients with renal impairment or collagen vascular disease, and that available data are insufficient to show that lisinopril does not have a similar risk (See WARNINGS).

In considering the use of lisinopril, it should be noted that in controlled clinical trials ACE inhibitors have an effect on blood pressure that is less in Black patients than in non-Blacks. In addition, ACE inhibitors have been associated with a higher rate of angioedema in Black than in non-Black patients (See WARNINGS, Anaphylactoid and Possibly Related Reactions).

CONTRAINDICATIONS

Lisinopril tablets are contraindicated in patients who are hypersensitive to this product and in patients with a history of angioedema related to previous treatment with an angiotensin converting enzyme inhibitor and in patients with hereditary or idiopathic angioedema.

Do not coadminister aliskiren with lisinopril in patients with diabetes (see PRECAUTIONS, Drug Interactions).

WARNINGS

Anaphylactoid and Possibly Related Reactions:

Presumably because angiotensin-converting enzyme inhibitors affect the metabolism of eicosanoids and polypeptides, including endogenous bradykinin, patients receiving ACE inhibitors (including lisinopril) may be subject to a variety of adverse reactions, some of them serious.

Head and Neck Angioedema:

Angioedema of the face, extremities, lips, tongue, glottis and/or larynx has been reported in patients treated with angiotensin converting enzyme inhibitors, including lisinopril. This may occur at any time during treatment. ACE inhibitors have been associated with a higher rate of angioedema in Black than in non-Black patients. Lisinopril should be promptly discontinued and appropriate therapy and monitoring should be provided until complete and sustained resolution of signs and symptoms has occurred. Even in those instances where swelling of only the tongue is involved, without respiratory distress, patients may require prolonged observation since treatment with antihistamines and corticosteroids may not be sufficient. Very rarely, fatalities have been reported due to angioedema associated with laryngeal edema or tongue edema. Patients with involvement of the tongue, glottis or larynx are likely to experience airway obstruction, especially those with a history of airway surgery. Where there is involvement of the tongue, glottis or larynx, likely to cause airway obstruction, appropriate therapy, e.g., subcutaneous epinephrine solution 1:1000 (0.3 mL to 0.5 mL) and/or measures necessary to ensure a patent airway should be promptly provided (See ADVERSE REACTIONS).

Intestinal Angioedema:

Intestinal angioedema has been reported in patients treated with ACE inhibitors. These patients presented with abdominal pain (with or without nausea or vomiting); in some cases there was no prior history of facial angioedema and C-1 esterase levels were normal. The angioedema was diagnosed by procedures including abdominal CT scan or ultrasound, or at surgery, and symptoms resolved after stopping the ACE inhibitor. Intestinal angioedema should be included in the differential diagnosis of patients on ACE inhibitors presenting with abdominal pain.

Patients with a history of angioedema unrelated to ACE inhibitor therapy may be at increased risk of angioedema while receiving an ACE inhibitor (See also INDICATIONS AND USAGE and CONTRAINDICATIONS).

Anaphylactoid Reactions During Desensitization:

Two patients undergoing desensitizing treatment with hymenoptera venom while receiving ACE inhibitors sustained life-threatening anaphylactoid reactions. In the same patients, these reactions were avoided when ACE inhibitors were temporarily withheld, but they reappeared upon inadvertent rechallenge.

Anaphylactoid Reactions During Membrane Exposure:

Sudden and potentially life threatening anaphylactoid reactions have been reported in some patients dialyzed with high-flux membranes (e.g., AN69®*) and treated concomitantly with an ACE inhibitor. In such patients, dialysis must be stopped immediately, and aggressive therapy for anaphylactoid reactions must be initiated. Symptoms have not been relieved by antihistamines in these situations. In these patients, consideration should be given to using a different type of dialysis membrane or a different class of antihypertensive agent. Anaphylactoid reactions have also been reported in patients undergoing low-density lipoprotein apheresis with dextran sulfate absorption.

*AN69 is a registered trademark of Hospal Ltd.

Hypotension:

Excessive hypotension is rare in patients with uncomplicated hypertension treated with lisinopril alone.

Patients with heart failure given lisinopril commonly have some reduction in blood pressure, with peak blood pressure reduction occurring 6 to 8 hours post dose. Evidence from the two-dose ATLAS trial suggested that incidence of hypotension may increase with dose of lisinopril in heart failure patients. Discontinuation of therapy because of continuing symptomatic hypotension usually is not necessary when dosing instructions are followed; caution should be observed when initiating therapy (See DOSAGE AND ADMINISTRATION).

Patients at risk of excessive hypotension, sometimes associated with oliguria and/or progressive azotemia, and rarely with acute renal failure and/or death, include those with the following conditions or characteristics: heart failure with systolic blood pressure below 100 mmHg, hyponatremia, high dose diuretic therapy, recent intensive diuresis or increase in diuretic dose, renal dialysis, or severe volume and/or salt depletion of any etiology. It may be advisable to eliminate the diuretic (except in patients with heart failure), reduce the diuretic dose or increase salt intake cautiously before initiating therapy with lisinopril in patients at risk for excessive hypotension who are able to tolerate such adjustments (See PRECAUTIONS, Drug Interactions and ADVERSE REACTIONS).

Patients with acute myocardial infarction in the GISSI-3 trial had a higher (9.0% versus 3.7%) incidence of persistent hypotension (systolic blood pressure < 90 mmHg for more than 1 hour) when treated with lisinopril. Treatment with lisinopril must not be initiated in acute myocardial infarction patients at risk of further serious hemodynamic deterioration after treatment with a vasodilator (e.g., systolic blood pressure of 100 mmHg or lower) or cardiogenic shock.

In patients at risk of excessive hypotension, therapy should be started under very close medical supervision and such patients should be followed closely for the first two weeks of treatment and whenever the dose of lisinopril and/or diuretic is increased. Similar considerations may apply to patients with ischemic heart or cerebrovascular disease, or in patients with acute myocardial infarction, in whom an excessive fall in blood pressure could result in a myocardial infarction or cerebrovascular accident.

If excessive hypotension occurs, the patient should be placed in the supine position and, if necessary, receive an intravenous infusion of normal saline. A transient hypotensive response is not a contraindication to further doses of lisinopril, which usually can be given without difficulty once the blood pressure has stabilized. If symptomatic hypotension develops, a dose reduction or discontinuation of lisinopril or concomitant diuretic may be necessary.

Leukopenia/Neutropenia/Agranulocytosis:

Another angiotensin-converting enzyme inhibitor, captopril, has been shown to cause agranulocytosis and bone marrow depression, rarely in uncomplicated patients but more frequently in patients with renal impairment especially if they also have a collagen vascular disease. Available data from clinical trials of lisinopril are insufficient to show that lisinopril does not cause agranulocytosis at similar rates. Marketing experience has revealed rare cases of leukopenia/neutropenia and bone marrow depression in which a causal relationship to lisinopril cannot be excluded. Periodic monitoring of white blood cell counts in patients with collagen vascular disease and renal disease should be considered.

Hepatic Failure:

Rarely, ACE inhibitors have been associated with a syndrome that starts with cholestatic jaundice or hepatitis and progresses to fulminant hepatic necrosis and (sometimes) death. The mechanism of this syndrome is not understood. Patients receiving ACE inhibitors who develop jaundice or marked elevations of hepatic enzymes should discontinue the ACE inhibitor and receive appropriate medical follow-up.

Fetal Toxicity

Pregnancy category D: Use of drugs that act on the renin-angiotensin system during the second and third trimesters of pregnancy reduces fetal renal function and increases fetal and neonatal morbidity and death. Resulting oligohydramnios can be associated with fetal lung hypoplasia and skeletal deformations. Potential neonatal adverse effects include skull hypoplasia, anuria, hypotension, renal failure, and death. When pregnancy is detected, discontinue lisinopril as soon as possible. These adverse outcomes are usually associated with use of these drugs in the second and third trimester of pregnancy. Most epidemiologic studies examining fetal abnormalities after exposure to antihypertensive use in the first trimester have not distinguished drugs affecting the renin-angiotensin system from other antihypertensive agents. Appropriate management of maternal hypertension during pregnancy is important to optimize outcomes for both mother and fetus.

In the unusual case that there is no appropriate alternative to therapy with drugs affecting the renin-angiotensin system for a particular patient, apprise the mother of the potential risk to the fetus. Perform serial ultrasound examinations to assess the intra-amniotic environment. If oligohydramnios is observed, discontinue lisinopril, unless it is considered lifesaving for the mother. Fetal testing may be appropriate, based on the week of pregnancy. Patients and physicians should be aware, however, that oligohydramnios may not appear until after the fetus has sustained irreversible injury. Closely observe infants with histories of in utero exposure to lisinopril for hypotension, oliguria, and hyperkalemia. (see PRECAUTIONS, Pediatric Use).

No teratogenic effects of lisinopril were seen in studies of pregnant rats, mice, and rabbits. On a mg/kg basis, the doses used were up to 625 times (in mice), 188 times (in rats), and 0.6 times (in rabbits) the maximum recommended human dose.

PRECAUTIONS

General

Aortic Stenosis/Hypertrophic Cardiomyopathy:

As with all vasodilators, lisinopril should be given with caution to patients with obstruction in the outflow tract of the left ventricle.

Impaired Renal Function:

As a consequence of inhibiting the renin-angiotensin-aldosterone system, changes in renal function may be anticipated in susceptible individuals. In patients with severe congestive heart failure whose renal function may depend on the activity of the renin-angiotensin-aldosterone system, treatment with angiotensin converting enzyme inhibitors, including lisinopril, may be associated with oliguria and/or progressive azotemia and rarely with acute renal failure and/or death.

In hypertensive patients with unilateral or bilateral renal artery stenosis, increases in blood urea nitrogen and serum creatinine may occur. Experience with another angiotensin-converting enzyme inhibitor suggests that these increases are usually reversible upon discontinuation of lisinopril and/or diuretic therapy. In such patients, renal function should be monitored during the first few weeks of therapy.

Some patients with hypertension or heart failure with no apparent pre-existing renal vascular disease have developed increases in blood urea nitrogen and serum creatinine, usually minor and transient, especially when lisinopril has been given concomitantly with a diuretic. This is more likely to occur in patients with pre-existing renal impairment. Dosage reduction and/or discontinuation of the diuretic and/or lisinopril may be required.

Patients with acute myocardial infarction in the GISSI-3 trial treated with lisinopril had a higher (2.4% versus 1.1%) incidence of renal dysfunction in-hospital and at six weeks (increasing creatinine concentration to over 3 mg/dL or a doubling or more of the baseline serum creatinine concentration). In acute myocardial infarction, treatment with lisinopril should be initiated with caution in patients with evidence of renal dysfunction, defined as serum creatinine concentration exceeding 2 mg/dL. If renal dysfunction develops during treatment with lisinopril (serum creatinine concentration exceeding 3 mg/dL or a doubling from the pre-treatment value) then the physician should consider withdrawal of lisinopril.

Evaluation of patients with hypertension, heart failure, or myocardial infarction should always include assessment of renal function (See DOSAGE AND ADMINISTRATION).

Hyperkalemia:

In clinical trials hyperkalemia (serum potassium greater than 5.7 mEq/L) occurred in approximately 2.2% of hypertensive patients and 4.8% of patients with heart failure. In most cases these were isolated values which resolved despite continued therapy. Hyperkalemia was a cause of discontinuation of therapy in approximately 0.1% of hypertensive patients; 0.6% of patients with heart failure and 0.1 % of patients with myocardial infarction. Risk factors for the development of hyperkalemia include renal insufficiency, diabetes mellitus, and the concomitant use of potassium-sparing diuretics, potassium supplements and/or potassium-containing salt substitutes. Hyperkalemia can cause serious, sometimes fatal, arrhythmias. Lisinopril should be used cautiously, if at all, with these agents and with frequent monitoring of serum potassium (See PRECAUTIONS, Drug Interactions).

Cough:

Presumably due to the inhibition of the degradation of endogenous bradykinin, persistent nonproductive cough has been reported with all ACE inhibitors, almost always resolving after discontinuation of therapy. ACE inhibitor-induced cough should be considered in the differential diagnosis of cough.

Surgery/Anesthesia:

In patients undergoing major surgery or during anesthesia with agents that produce hypotension, lisinopril may block angiotensin II formation secondary to compensatory renin release. If hypotension occurs and is considered to be due to this mechanism, it can be corrected by volume expansion.

Information for Patients

Angioedema: Angioedema, including laryngeal edema may occur at any time during treatment with angiotensin-converting enzyme inhibitors, including lisinopril. Patients should be so advised and told to report immediately any signs or symptoms suggesting angioedema (swelling of face, extremities, eyes, lips, tongue, difficulty in swallowing or breathing) and to take no more drug until they have consulted with the prescribing physician.

Symptomatic Hypotension: Patients should be cautioned to report lightheadedness especially during the first few days of therapy. If actual syncope occurs, the patient should be told to discontinue the drug until they have consulted with the prescribing physician.

All patients should be cautioned that excessive perspiration and dehydration may lead to an excessive fall in blood pressure because of reduction in fluid volume. Other causes of volume depletion such as vomiting or diarrhea may also lead to a fall in blood pressure; patients should be advised to consult with their physician.

Hyperkalemia: Patients should be told not to use salt substitutes containing potassium without consulting their physician.

Hypoglycemia: Diabetic patients treated with oral antidiabetic agents or insulin starting an ACE inhibitor should be told to closely monitor for hypoglycemia, especially during the first month of combined use (See PRECAUTIONS, Drug Interactions).

Leukopenia/Neutropenia: Patients should be told to report promptly any indication of infection (e.g., sore throat, fever) which may be a sign of leukopenia/neutropenia.

Pregnancy: Female patients of childbearing age should be told about the consequences of exposure to lisinopril during pregnancy. Discuss treatment options with women planning to become pregnant. Patients should be asked to report pregnancies to their physicians as soon as possible.

NOTE: As with many other drugs, certain advice to patients being treated with lisinopril is warranted. This information is intended to aid in the safe and effective use of this medication. It is not a disclosure of all possible adverse or intended effects.

Drug Interactions

Hypotension - Patients on Diuretic Therapy: Patients on diuretics and especially those in whom diuretic therapy was recently instituted, may occasionally experience an excessive reduction of blood pressure after initiation of therapy with lisinopril. The possibility of hypotensive effects with lisinopril can be minimized by either discontinuing the diuretic or increasing the salt intake prior to initiation of treatment with lisinopril. If it is necessary to continue the diuretic, initiate therapy with lisinopril at a dose of 5 mg daily, and provide close medical supervision after the initial dose until blood pressure has stabilized (See WARNINGS and DOSAGE AND ADMINISTRATION). When a diuretic is added to the therapy of a patient receiving lisinopril, an additional antihypertensive effect is usually observed. Studies with ACE inhibitors in combination with diuretics indicate that the dose of the ACE inhibitor can be reduced when it is given with a diuretic (See DOSAGE AND ADMINISTRATION).

Antidiabetics: Epidemiological studies have suggested that concomitant administration of ACE inhibitors and antidiabetic medicines (insulins, oral hypoglycemic agents) may cause an increased blood-glucose-lowering effect with risk of hypoglycemia. This phenomenon appeared to be more likely to occur during the first weeks of combined treatment and in patients with renal impairment. In diabetic patients treated with oral antidiabetic agents or insulin, glycemic control should be closely monitored for hypoglycemia, especially during the first month of treatment with an ACE inhibitor.

Non-Steroidal Anti-Inflammatory Agents including Selective Cyclooxygenase-2 Inhibitors (COX-2 Inhibitors): In patients who are elderly, volume-depleted (including those on diuretic therapy), or with compromised renal function, coadministration of NSAIDs, including selective COX-2 inhibitors, with ACE inhibitors, including lisinopril, may result in deterioration of renal function, including possible acute renal failure. These effects are usually reversible. Monitor renal function periodically in patients receiving lisinopril and NSAID therapy.

The antihypertensive effect of ACE inhibitors, including lisinopril, may be attenuated by NSAIDs.

Dual Blockade of the Renin-Angiotensin System (RAS): Dual blockade of the RAS with angiotensin receptor blockers, ACE inhibitors, or aliskiren is associated with increased risks of hypotension, hyperkalemia, and changes in renal function (including acute renal failure) compared to monotherapy. Closely monitor blood pressure, renal function and electrolytes in patients on lisinopril and other agents that affect the RAS.

Do not coadminister aliskiren with lisinopril in patients with diabetes. Avoid use of aliskiren with lisinopril in patients with renal impairment (GFR < 60 ml/min).

Other Agents: Lisinopril has been used concomitantly with nitrates and/or digoxin without evidence of clinically significant adverse interactions. This included post myocardial infarction patients who were receiving intravenous or transdermal nitroglycerin. No clinically important pharmacokinetic interactions occurred when lisinopril was used concomitantly with propranolol or hydrochlorothiazide. The presence of food in the stomach does not alter the bioavailability of lisinopril.

Agents Increasing Serum Potassium: Lisinopril attenuates potassium loss caused by thiazide-type diuretics. Use of lisinopril with potassium-sparing diuretics (e.g., spironolactone, eplerenone, triamterene or amiloride), potassium supplements, or potassium-containing salt substitutes may lead to significant increases in serum potassium. Therefore, if concomitant use of these agents is indicated because of demonstrated hypokalemia, they should be used with caution and with frequent monitoring of serum potassium. Potassium-sparing agents should generally not be used in patients with heart failure who are receiving lisinopril.

Lithium: Lithium toxicity has been reported in patients receiving lithium concomitantly with drugs which cause elimination of sodium, including ACE inhibitors. Lithium toxicity was usually reversible upon discontinuation of lithium and the ACE inhibitor. It is recommended that serum lithium levels be monitored frequently if lisinopril is administered concomitantly with lithium.

Gold: Nitritoid reactions (symptoms include facial flushing, nausea, vomiting and hypotension) have been reported rarely in patients on therapy with injectable gold (sodium aurothiomalate) and concomitant ACE inhibitor therapy including lisinopril.

Carcinogenesis, Mutagenesis, Impairment of Fertility

There was no evidence of a tumorigenic effect when lisinopril was administered for 105 weeks to male and female rats at doses up to 90 mg/kg/day (about 56 or 9 times* the maximum recommended daily human dose, based on body weight and body surface area, respectively). There was no evidence of carcinogenicity when lisinopril was administered for 92 weeks to (male and female) mice at doses up to 135 mg/kg/day (about 84 times* the maximum recommended daily human dose). This dose was 6.8 times the maximum human dose based on body surface area in mice.

Lisinopril was not mutagenic in the Ames microbial mutagen test with or without metabolic activation. It was also negative in a forward mutation assay using Chinese hamster lung cells. Lisinopril did not produce single strand DNA breaks in an in vitro alkaline elution rat hepatocyte assay. In addition, lisinopril did not produce increases in chromosomal aberrations in an in vitro test in Chinese hamster ovary cells or in an in vivo study in mouse bone marrow.

There were no adverse effects on reproductive performance in male and female rats treated with up to 300 mg/kg/day of lisinopril. This dose is 188 times and 30 times the maximum human dose when based on mg/kg and mg/m^2, respectively.

* Calculations assume a human weight of 50 kg and human body surface area of 1.62 m^2.

Nursing Mothers:

Milk of lactating rats contains radioactivity following administration of ^14C lisinopril. It is not known whether this drug is excreted in human milk. Because many drugs are excreted in human milk and because of the potential for serious adverse reactions in nursing infants from ACE inhibitors, a decision should be made whether to discontinue nursing or discontinue lisinopril, taking into account the importance of the drug to the mother.

Pediatric Use

Neonates with a history of in utero exposure to lisinopril:
If oliguria or hypotension occurs, direct attention toward support of blood pressure and renal perfusion. Exchange transfusions or dialysis may be required as a means of reversing hypotension and/or substituting for disordered renal function. Lisinopril, which crosses the placenta, has been removed from neonatal circulation by peritoneal dialysis with some clinical benefit, and theoretically may be removed by exchange transfusion, although there is no experience with the latter procedure.

Antihypertensive effects of lisinopril have been established in hypertensive pediatric patients aged 6 to 16 years.

There are no data on the effect of lisinopril on blood pressure in pediatric patients under age 6 or in pediatric patients with glomerular filtration rate < 30 mL/min/1.73 m^2 (See CLINICAL PHARMACOLOGY, Pharmacokinetics and Metabolism and Pharmacodynamics and Clinical Effects, and DOSAGE AND ADMINISTRATION).

Geriatric Use:

Clinical studies of lisinopril in patients with hypertension did not include sufficient numbers of subjects aged 65 and over to determine whether they respond differently from younger subjects. Other clinical experience in this population has not identified differences in responses between the elderly and younger patients. In general, dose selection for an elderly patient should be cautious, usually starting at the low end of the dosing range, reflecting the greater frequency of decreased hepatic, renal, or cardiac function, and of concomitant disease or other drug therapy.

In the ATLAS trial of lisinopril in patients with congestive heart failure, 1,596 (50%) were 65 and over, while 437 (14%) were 75 and over. In a clinical study of lisinopril in patients with myocardial infarctions 4,413 (47%) were 65 and over, while 1,656 (18%) were 75 and over. In these studies, no overall differences in safety or effectiveness were observed between elderly and younger patients, and other reported clinical experiences has not identified differences in responses between the elderly and younger patients (See CLINICAL PHARMACOLOGY, Pharmacodynamics and Clinical Effects, Heart Failure and CLINICAL PHARMACOLOGY, Pharmacodynamics and Clinical Effects, Acute Myocardial Infarction).

Other reported clinical experience has not identified differences in responses between elderly and younger patients, but greater sensitivity of some older individuals cannot be ruled out.

Pharmacokinetic studies indicate that maximum blood levels and area under the plasma concentration time curve (AUC) are doubled in older patients (See CLINICAL PHARMACOLOGY, Pharmacokinetics and Metabolism).

This drug is known to be substantially excreted by the kidney, and the risk of toxic reactions to this drug may be greater in patients with impaired renal function. Because elderly patients are more likely to have decreased renal function, care should be taken in dose selection. Evaluation of patients with hypertension, congestive heart failure, or myocardial infarction should always include assessment of renal function (See DOSAGE AND ADMINISTRATION).

This product contains FD&C Yellow No.5 (tartrazine) which may cause allergic-type reactions (including bronchial asthma) in certain susceptible persons. Although the overall incidence of FD&C Yellow No.5 (tartrazine) sensitivity in the general population is low, it is frequently seen in patients who also have aspirin hypersensitivity.

ADVERSE REACTIONS

Lisinopril has been found to be generally well tolerated in controlled clinical trials involving 1969 patients with hypertension or heart failure. For the most part, adverse experiences were mild and transient.

Hypertension

In clinical trials in patients with hypertension treated with lisinopril, discontinuation of therapy due to clinical adverse experiences occurred in 5.7% of patients. The overall frequency of adverse experiences could not be related to total daily dosage within the recommended therapeutic dosage range.

For adverse experiences occurring in greater than 1% of patients with hypertension treated with lisinopril or lisinopril plus hydrochlorothiazide in controlled clinical trials, and more frequently with lisinopril and/or lisinopril plus hydrochlorothiazide than placebo, comparative incidence data are listed in the table below:

PERCENT OF PATIENTS IN CONTROLLED STUDIES
 | LISINOPRIL (n=1349) Incidence (discontinuation) | LISINOPRIL/HCTZ (n=629) Incidence (discontinuation) | PLACEBO (n=207) Incidence (discontinuation)
Body as a Whole
Fatigue | 2.5 (0.3) | 4.0 (0.5) | 1.0 (0.0)
Asthenia | 1.3 (0.5) | 2.1 (0.2) | 1.0 (0.0)
Orthostatic Effects | 1.2 (0.0) | 3.5 (0.2) | 1.0 (0.0)
Cardiovascular
Hypotension | 1.2 (0.5) | 1.6 (0.5) | 0.5 (0.5)
Digestive
Diarrhea | 2.7 (0.2) | 2.7 (0.3) | 2.4 (0.0)
Nausea | 2.0 (0.4) | 2.5 (0.2) | 2.4 (0.0)
Vomiting | 1.1 (0.2) | 1.4 (0.1) | 0.5 (0.0)
Dyspepsia | 0.9 (0.0) | 1.9 (0.0) | 0.0 (0.0)
Musculoskeletal
Muscle Cramps | 0.5 (0.0) | 2.9 (0.8) | 0.5 (0.0)
Nervous/Psychiatric
Headache | 5.7 (0.2) | 4.5 (0.5) | 1.9 (0.0)
Dizziness | 5.4 (0.4) | 9.2 (1.0) | 1.9 (0.0)
Paresthesia | 0.8 (0.1) | 2.1 (0.2) | 0.0 (0.0)
Decreased Libido | 0.4 (0.1) | 1.3 (0.1) | 0.0 (0.0)
Vertigo | 0.2 (0.1) | 1.1 (0.2) | 0.0 (0.0)
Respiratory
Cough | 3.5 (0.7) | 4.6 (0.8) | 1.0 (0.0)
Upper Respiratory Infection | 2.1 (0.1) | 2.7 (0.1) | 0.0 (0.0)
Common Cold | 1.1 (0.1) | 1.3 (0.1) | 0.0 (0.0)
Nasal Congestion | 0.4 (0.1) | 1.3 (0.1) | 0.0 (0.0)
Influenza | 0.3 (0.1) | 1.1 (0.1) | 0.0 (0.0)
Skin
Rash | 1.3 (0.4) | 1.6 (0.2) | 0.5 (0.5)
Urogenital
Impotence | 1.0 (0.4) | 1.6 (0.5) | 0.0 (0.0)

Chest pain and back pain were also seen, but were more common on placebo than lisinopril.

Heart Failure

In patients with heart failure treated with lisinopril for up to four years, discontinuation of therapy due to clinical adverse experiences occurred in 11.0% of patients. In controlled studies in patients with heart failure, therapy was discontinued in 8.1% of patients treated with lisinopril for 12 weeks, compared to 7.7% of patients treated with placebo for 12 weeks.

The following table lists those adverse experiences which occurred in greater than 1% of patients with heart failure treated with lisinopril or placebo for up to 12 weeks in controlled clinical trials, and more frequently on lisinopril than placebo.

 | Controlled Trials
 | Lisinopril (n=407) Incidence (discontinuation) 12 weeks | Placebo (n=155) Incidence (discontinuation) 12 weeks
Body as a Whole
Chest Pain | 3.4 (0.2) | 1.3 (0.0)
Abdominal Pain | 2.2 (0.7) | 1.9 (0.0)
Cardiovascular
Hypotension | 4.4 (1.7) | 0.6 (0.6)
Digestive
Diarrhea | 3.7 (0.5) | 1.9 (0.0)
Nervous/Psychiatric
Dizziness | 11.8 (1.2) | 4.5 (1.3)
Headache | 4.4 (0.2) | 3.9 (0.0)
Respiratory
Upper Respiratory Infection | 1.5 (0.0) | 1.3 (0.0)
Skin
Rash | 1.7 (0.5) | 0.6 (0.6)

Also observed at > 1% with lisinopril but more frequent or as frequent on placebo than lisinopril in controlled trials were asthenia, angina pectoris, nausea, dyspnea, cough, and pruritus.

Worsening of heart failure, anorexia, increased salivation, muscle cramps, back pain, myalgia, depression, chest sound abnormalities, and pulmonary edema were also seen in controlled clinical trials, but were more common on placebo than lisinopril.

In the two-dose ATLAS trial in heart failure patients, withdrawals due to adverse events were not different between the low and high groups, either in total number of discontinuation (17-18%) or in rare specific events (<1%). The following adverse events, mostly related to ACE inhibition, were reported more commonly in the high dose group:

% of patients Events | High Dose (N=1568) | Low Dose (N=1596)
Dizziness | 18.9 | 12.1
Hypotension | 10.8 | 6.7
Creatinine increased | 9.9 | 7.0
Hyperkalemia | 6.4 | 3.5
NPN * increased | 9.2 | 6.5
Syncope | 7.0 | 5.1
* NPN = non-protein nitrogen

Acute Myocardial Infarction

In the GISSI-3 trial, in patients treated with lisinopril for six weeks following acute myocardial infarction, discontinuation of therapy occurred in 17.6% of patients.

Patients treated with lisinopril had a significantly higher incidence of hypotension and renal dysfunction compared with patients not taking lisinopril.

In the GISSI-3 trial, hypotension (9.7%), renal dysfunction (2.0%), cough (0.5%), post infarction angina (0.3%), skin rash and generalized edema (0.01%), and angioedema (0.01%) resulted in withdrawal of treatment. In elderly patients treated with lisinopril, discontinuation due to renal dysfunction was 4.2%.

Other clinical adverse experiences occurring in 0.3% to 1.0% of patients with hypertension or heart failure treated with lisinopril in controlled clinical trials and rarer, serious, possibly drug-related events reported in uncontrolled studies or marketing experience are listed below, and within each category are in order of decreasing severity:

Body as a Whole: Anaphylactoid reactions (See WARNINGS, Anaphylactoid and Possibly Related Reactions), syncope, orthostatic effects, chest discomfort, pain, pelvic pain, flank pain, edema, facial edema, virus infection, fever, chills, malaise.

Cardiovascular: Cardiac arrest; myocardial infarction or cerebrovascular accident possibly secondary to excessive hypotension in high risk patients (See WARNINGS, Hypotension); pulmonary embolism and infarction, arrhythmias (including ventricular tachycardia, atrial tachycardia, atrial fibrillation, bradycardia and premature ventricular contractions), palpitations, transient ischemic attacks, paroxysmal nocturnal dyspnea, orthostatic hypotension, decreased blood pressure, peripheral edema, vasculitis.

Digestive: Pancreatitis, hepatitis (hepatocellular or cholestatic jaundice) (See WARNINGS, Hepatic Failure), vomiting, gastritis, dyspepsia, heartburn, gastrointestinal cramps, constipation, flatulence, dry mouth.

Hematologic: Rare cases of bone marrow depression, hemolytic anemia, leukopenia/neutropenia and thrombocytopenia.

Endocrine: Diabetes mellitus, inappropriate antidiuretic hormone secretion.

Metabolic: Weight loss, dehydration, fluid overload, gout, weight gain.

Cases of hypoglycemia in diabetic patients on oral antidiabetic agents or insulin have been reported in post-marketing experience (See PRECAUTIONS, Drug Interactions).

Musculoskeletal: Arthritis, arthralgia, neck pain, hip pain, low back pain, joint pain, leg pain, knee pain, shoulder pain, arm pain, lumbago.

Nervous System/Psychiatric: Stroke, ataxia, memory impairment, tremor, peripheral neuropathy (e.g., dysesthesia), spasm, paresthesia, confusion, insomnia, somnolence, hypersomnia, irritability, nervousness, mood alterations (including depressive symptoms) and hallucinations.

Respiratory System: Malignant lung neoplasms, hemoptysis, pulmonary infiltrates, bronchospasm, asthma, pleural effusion, pneumonia, eosinophilic pneumonitis, bronchitis, wheezing, orthopnea, painful respiration, epistaxis, laryngitis, sinusitis, pharyngeal pain, pharyngitis, rhinitis, rhinorrhea.

Skin: Urticaria, alopecia, herpes zoster, photosensitivity, skin lesions, skin infections, pemphigus, erythema, flushing, diaphoresis, cutaneous pseudolymphoma, psoriasis. Other severe skin reactions have been reported rarely, including toxic epidermal necrolysis and Stevens-Johnson Syndrome; causal relationship has not been established.

Special Senses: Visual loss, diplopia, blurred vision, tinnitus, photophobia, taste disturbances, olfactory disturbance.

Urogenital System: Acute renal failure, oliguria, anuria, uremia, progressive azotemia, renal dysfunction (See PRECAUTIONS and DOSAGE AND ADMINISTRATION), pyelonephritis, dysuria, urinary tract infection, breast pain.

Miscellaneous: A symptom complex has been reported which may include a positive ANA, an elevated erythrocyte sedimentation rate, arthralgia/arthritis, myalgia, fever, vasculitis, eosinophilia and leukocytosis. Rash, photosensitivity or other dermatological manifestations may occur alone or in combination with these symptoms.

Angioedema: Angioedema has been reported in patients receiving lisinopril with an incidence higher in Black than in non-Black patients. Angioedema associated with laryngeal edema may be fatal. If angioedema of the face, extremities, lips, tongue, glottis and/or larynx occurs, treatment with lisinopril should be discontinued and appropriate therapy instituted immediately (See WARNINGS).

In rare cases, intestinal angioedema has been reported in postmarketing experience.

Hypotension: In hypertensive patients, hypotension occurred in 1.2% and syncope occurred in 0.1% of patients with an incidence higher in Black than in non-Black patients. Hypotension or syncope was a cause of discontinuation of therapy in 0.5% of hypertensive patients. In patients with heart failure, hypotension occurred in 5.3% and syncope occurred in 1.8% of patients. These adverse experiences were possibly dose-related (see above data from ATLAS Trial) and caused discontinuation of therapy in 1.8% of these patients in the symptomatic trials. In patients treated with lisinopril for six weeks after acute myocardial infarction, hypotension (systolic blood pressure ≤100 mmHg) resulted in discontinuation of therapy in 9.7% of the patients (See WARNINGS).

Cough: See PRECAUTIONS, Cough

Pediatric Patients: No relevant differences between the adverse experience profile for pediatric patients and that previously reported for adult patients were identified.

Clinical Laboratory Test Findings

Serum Electrolytes: Hyperkalemia (See PRECAUTIONS), hyponatremia.

Creatinine, Blood Urea Nitrogen: Minor increases in blood urea nitrogen and serum creatinine, reversible upon discontinuation of therapy, were observed in about 2.0% of patients with essential hypertension treated with lisinopril alone. Increases were more common in patients receiving concomitant diuretics and in patients with renal artery stenosis (See PRECAUTIONS). Reversible minor increases in blood urea nitrogen and serum creatinine were observed in approximately 11.6% of patients with heart failure on concomitant diuretic therapy. Frequently, these abnormalities resolved when the dosage of the diuretic was decreased.

Hemoglobin and Hematocrit: Small decreases in hemoglobin and hematocrit (mean decreases of approximately 0.4 g% and 1.3 vol%, respectively) occurred frequently in patients treated with lisinopril but were rarely of clinical importance in patients without some other cause of anemia. In clinical trials, less than 0.1% of patients discontinued therapy due to anemia. Hemolytic anemia has been reported; a causal relationship to lisinopril cannot be excluded.

Liver Function Tests: Rarely, elevations of liver enzymes and/or serum bilirubin have occurred, (See WARNINGS, Hepatic Failure).

In hypertensive patients, 2.0% discontinued therapy due to laboratory adverse experiences, principally elevations in blood urea nitrogen (0.6%), serum creatinine (0.5%) and serum potassium (0.4%).

In the heart failure trials, 3.4% of patients discontinued therapy due to laboratory adverse experiences; 1.8% due to elevations in blood urea nitrogen and/or creatinine and 0.6% due to elevations in serum potassium.

In the myocardial infarction trial, 2.0% of patients receiving lisinopril discontinued therapy due to renal dysfunction (increasing creatinine concentration to over 3 mg/dL or a doubling or more of the baseline serum creatinine concentration); less than 1.0% of patients discontinued therapy due to other laboratory adverse experiences: 0.1% with hyperkalemia and less than 0.1% with hepatic enzyme alterations.

OVERDOSAGE

Following a single oral dose of 20 g/kg no lethality occurred in rats, and death occurred in one of 20 mice receiving the same dose. The most likely manifestation of overdosage would be hypotension, for which the usual treatment would be intravenous infusion of normal saline solution.

Lisinopril can be removed by hemodialysis (See WARNINGS, Anaphylactoid Reactions During Membrane Exposure).

DOSAGE AND ADMINISTRATION

Hypertension

Initial Therapy: In patients with uncomplicated essential hypertension not on diuretic therapy, the recommended initial dose is 10 mg once a day. Dosage should be adjusted according to blood pressure response. The usual dosage range is 20 to 40 mg per day administered in a single daily dose. The antihypertensive effect may diminish toward the end of the dosing interval regardless of the administered dose, but most commonly with a dose of 10 mg daily. This can be evaluated by measuring blood pressure just prior to dosing to determine whether satisfactory control is being maintained for 24 hours. If it is not, an increase in dose should be considered. Doses up to 80 mg have been used but do not appear to give greater effect. If blood pressure is not controlled with lisinopril alone, a low dose of a diuretic may be added. Hydrochlorothiazide, 12.5 mg has been shown to provide an additive effect. After the addition of a diuretic, it may be possible to reduce the dose of lisinopril.

Diuretic Treated Patients: In hypertensive patients who are currently being treated with a diuretic, symptomatic hypotension may occur occasionally following the initial dose of lisinopril. The diuretic should be discontinued, if possible, for two to three days before beginning therapy with lisinopril tablet to reduce the likelihood of hypotension (See WARNINGS). The dosage of lisinopril should be adjusted according to blood pressure response. If the patient's blood pressure is not controlled with lisinopril alone, diuretic therapy may be resumed as described above.

If the diuretic cannot be discontinued, an initial dose of 5 mg should be used under medical supervision for at least two hours and until blood pressure has stabilized for at least an additional hour (See WARNINGS and PRECAUTIONS, Drug Interactions).

Concomitant administration of lisinopril with potassium supplements, potassium salt substitutes, or potassium-sparing diuretics may lead to increases of serum potassium (See PRECAUTIONS).

Dosage Adjustment in Renal Impairment: The usual dose of lisinopril (10 mg) is recommended for patients with creatinine clearance > 30 mL/min (serum creatinine of up to approximately 3 mg/dL). For patients with creatinine clearance ≥ 10 mL/min ≤ 30 mL/min (serum creatinine ≥ 3 mg/dL), the first dose is 5 mg once daily. For patients with creatinine clearance < 10 mL/min (usually on hemodialysis) the recommended initial dose is 2.5 mg. The dosage may be titrated upward until blood pressure is controlled or to a maximum of 40 mg daily.

Renal Status | Creatinine Clearance mL/min | Initial Dose mg/day
Normal Renal Function to Mild Impairment | >30 | 10
Moderate to Severe Impairment | ≥10 ≤30 | 5
Dialysis Patients* | < 10 | 2.5* *
*See WARNINGS, Anaphylactoid Reactions During Membrane Exposure.
* * Dosage or dosing interval should be adjusted depending on the blood pressure response.

Heart Failure

Lisinopril tablets are indicated as adjunctive therapy with diuretics and (usually) digitalis. The recommended starting dose is 5 mg once a day. When initiating treatment with lisinopril in patients with heart failure, the initial dose should be administered under medical observation, especially in those patients with low blood pressure (systolic blood pressure below 100 mmHg). The mean peak blood pressure lowering occurs six to eight hours after dosing. Observation should continue until blood pressure is stable. The concomitant diuretic dose should be reduced, if possible, to help minimize hypovolemia which may contribute to hypotension (See WARNINGS and PRECAUTIONS, Drug Interactions). The appearance of hypotension after the initial dose of lisinopril does not preclude subsequent careful dose titration with the drug, following effective management of the hypotension.

The usual effective dosage range is 5 to 40 mg per day administered as a single daily dose. The dose of lisinopril can be increased by increments of no greater than 10 mg, at intervals of no less than 2 weeks to the highest tolerated dose, up to a maximum of 40 mg daily. Dose adjustment should be based on the clinical response of individual patients.

Dosage Adjustment in Patients with Heart Failure and Renal Impairment or Hyponatremia: In patients with heart failure who have hyponatremia (serum sodium < 130 mEq/L) or moderate to severe renal impairment (creatinine clearance ≤ 30 mL/min or serum creatinine > 3 mg/dL), therapy with lisinopril should be initiated at a dose of 2.5 mg once a day under close medical supervision (See WARNINGS and PRECAUTIONS, Drug Interactions).

Acute Myocardial Infarction

In hemodynamically stable patients within 24 hours of the onset of symptoms of acute myocardial infarction, the first dose of lisinopril is 5 mg given orally, followed by 5 mg after 24 hours, 10 mg after 48 hours and then 10 mg of lisinopril once daily. Dosing should continue for six weeks. Patients should receive, as appropriate, the standard recommended treatments such as thrombolytics, aspirin, and beta-blockers.

Patients with a low systolic blood pressure (≤ 120 mmHg) when treatment is started or during the first 3 days after the infarct should be given a lower 2.5 mg oral dose of lisinopril tablet (See WARNINGS). If hypotension occurs (systolic blood pressure ≤ 100 mmHg) a daily maintenance dose of 5 mg may be given with temporary reductions to 2.5 mg if needed. If prolonged hypotension occurs (systolic blood pressure < 90 mmHg for more than 1 hour) lisinopril tablet should be withdrawn. For patients who develop symptoms of heart failure, see DOSAGE AND ADMINISTRATION, Heart Failure.

Dosage Adjustment in Patients With Myocardial Infarction with Renal Impairment: In acute myocardial infarction, treatment with lisinopril tablets should be initiated with caution in patients with evidence of renal dysfunction, defined as serum creatinine concentration exceeding 2 mg/dL. No evaluation of dosing adjustments in myocardial infarction patients with severe renal impairment has been performed.

Use in Elderly

In general, the clinical response was similar in younger and older patients given similar doses of lisinopril. Pharmacokinetic studies, however, indicate that maximum blood levels and area under the plasma concentration time curve (AUC) are doubled in older patients, so that dosage adjustments should be made with particular caution.

Pediatric Hypertensive Patients ≥ 6 years of age

The usual recommended starting dose is 0.07 mg/kg once daily (up to 5 mg total). Dosage should be adjusted according to blood pressure response. Doses above 0.61 mg/kg (or in excess of 40 mg) have not been studied in pediatric patients (See CLINICAL PHARMACOLOGY, Pharmacokinetics and Metabolism and Pharmacodynamics and Clinical Effects).

Lisinopril is not recommended in pediatric patients < 6 years or in pediatric patients with glomerular filtration rate < 30 mL/min/1.73 m^2 (See CLINICAL PHARMACOLOGY, Pharmacokinetics and Metabolism and Pharmacodynamics and Clinical Effects and PRECAUTIONS).

HOW SUPPLIED

Lisinopril Tablets USP 2.5 mg, 5 mg, 10 mg, 20 mg, 30 mg and 40 mg are supplied as follows:

20 mg Tablets: Yellow, round, unscored, flat-faced, beveled-edge tablets, debossed “WATSON”and “408”on the periphery of one side and plain on the other side, in bottles of 30, 60, 90, and 100.

Storage

Store at 20º to 25ºC (68º to 77ºF) [See USP Controlled Room Temperature]. Protect from moisture, freezing and excessive heat. Dispense in a tight container as defined in the USP.

Manufactured by:
Watson Pharma Private Limited
Verna, Salcette Goa 403 722 INDIA

Distributed by:
Watson Pharma, Inc.
Parsippany, NJ 07054 USA

Revised: January 2014

Repackaged by:

Proficient Rx LP
Thousand Oaks, CA 91320